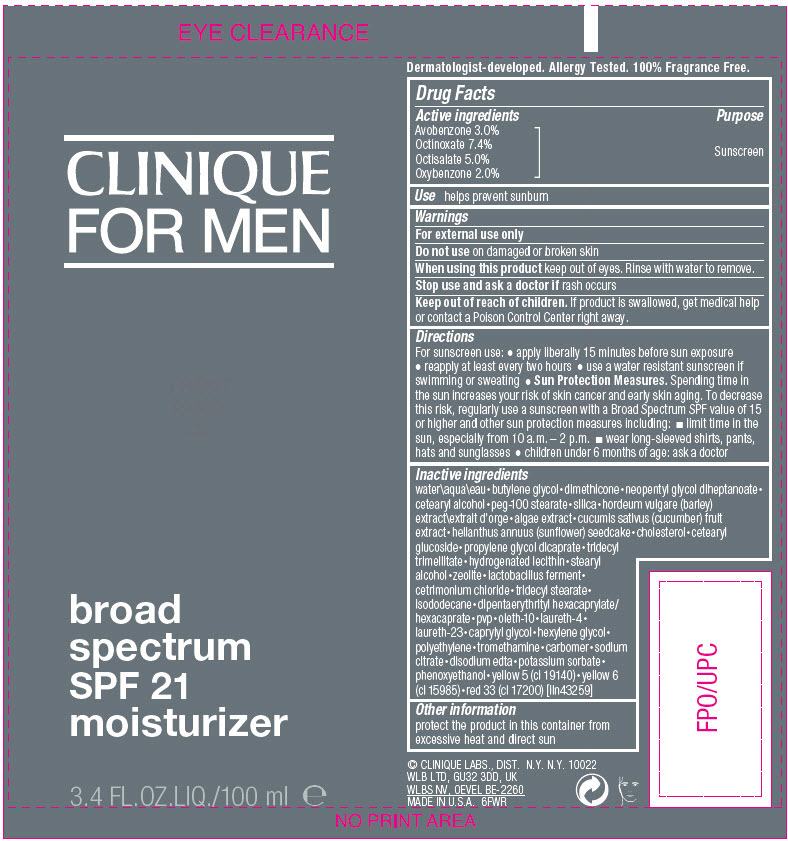 DRUG LABEL: CLINIQUE FOR MEN BROAD SPECTRUM SPF 21 MOISTURIZER
NDC: 49527-081 | Form: LOTION
Manufacturer: CLINIQUE LABORATORIES LLC
Category: otc | Type: HUMAN OTC DRUG LABEL
Date: 20231020

ACTIVE INGREDIENTS: AVOBENZONE 30 mg/1 mL; OCTINOXATE 74 mg/1 mL; OCTISALATE 50 mg/1 mL; OXYBENZONE 20 mg/1 mL
INACTIVE INGREDIENTS: FD&C YELLOW NO. 5; FD&C YELLOW NO. 6; D&C RED NO. 33; AGAR, UNSPECIFIED; ZEOLITE A; LIMOSILACTOBACILLUS REUTERI; CETRIMONIUM CHLORIDE; WATER; BUTYLENE GLYCOL; DIMETHICONE; NEOPENTYL GLYCOL DIHEPTANOATE; CETOSTEARYL ALCOHOL; PEG-100 STEARATE; SILICA, TRIMETHYLSILYL CAPPED; BARLEY; CUCUMBER; HELIANTHUS ANNUUS SEEDCAKE; CHOLESTEROL; CETEARYL GLUCOSIDE; PROPYLENE GLYCOL DICAPRATE; TRIDECYL TRIMELLITATE; HYDROGENATED SOYBEAN LECITHIN; STEARYL ALCOHOL; TRIDECYL STEARATE; ISODODECANE; DIPENTAERYTHRITYL HEXACAPRYLATE/HEXACAPRATE; POVIDONE, UNSPECIFIED; OLETH-10; LAURETH-4; LAURETH-23; CAPRYLYL GLYCOL; HEXYLENE GLYCOL; HIGH DENSITY POLYETHYLENE; TROMETHAMINE; CARBOMER HOMOPOLYMER, UNSPECIFIED TYPE; SODIUM CITRATE, UNSPECIFIED FORM; EDETATE DISODIUM ANHYDROUS; POTASSIUM SORBATE; PHENOXYETHANOL

CLINIQUE FOR MEN BROAD SPECTRUM SPF 21 MOISTURIZER

Drug Facts

Active ingredients

Avobenzone 3.0%
Octinoxate 7.4%
Octisalate 5.0%
Oxybenzone 2.0%

Purpose

Sunscreen

Use

helps prevent sunburn

Warnings

For external use only

Do not use on damaged or broken skin

When using this product keep out of eyes. Rinse with water to remove.

Stop use and ask a doctor if rash occurs

Keep out of reach of children. If product is swallowed, get medical help or contact a Poison Control Center right away.

Directions

For sunscreen use:

- apply liberally 15 minutes before sun exposure
- reapply at least every two hours
- use a water resistant sunscreen if swimming or sweating
- Sun Protection Measures. Spending time in the sun increases your risk of skin cancer and early skin aging. To decrease this risk, regularly use a sunscreen with a Broad Spectrum SPF value of 15 or higher and other sun protection measures including:
  - limit time in the sun, especially from 10 a.m. – 2 p.m.
  - wear long-sleeved shirts, pants, hats and sunglasses
- children under 6 months of age: ask a doctor

Inactive ingredients

water\aqua\eau•butylene glycol•dimethicone•neopentyl glycol diheptanoate•cetearyl alcohol•peg-100 stearate•silica•hordeum vulgare (barley) extract\extrait d'orge•algae extract•cucumis sativus (cucumber) fruit extract•helianthus annuus (sunflower) seedcake•cholesterol•cetearyl glucoside•propylene glycol dicaprate•tridecyl trimellitate•hydrogenated lecithin•stearyl alcohol•zeolite•lactobacillus ferment•cetrimonium chloride•tridecyl stearate•isododecane•dipentaerythrityl hexacaprylate/hexacaprate•pvp•oleth-10•laureth-4•laureth-23•caprylyl glycol•hexylene glycol•polyethylene•tromethamine•carbomer•sodium citrate•disodium edta•potassium sorbate•phenoxyethanol•yellow 5 (ci 19140)•yellow 6 (ci 15985)•red 33 (ci 17200) [iln43259]

Other information

protect the product in this container from excessive heat and direct sun

PRINCIPAL DISPLAY PANEL - 100 mL Tube Label

CLINIQUE
FOR MEN

broad
spectrum
SPF 21
moisturizer

3.4 FL.OZ.LIQ./100 ml ℮